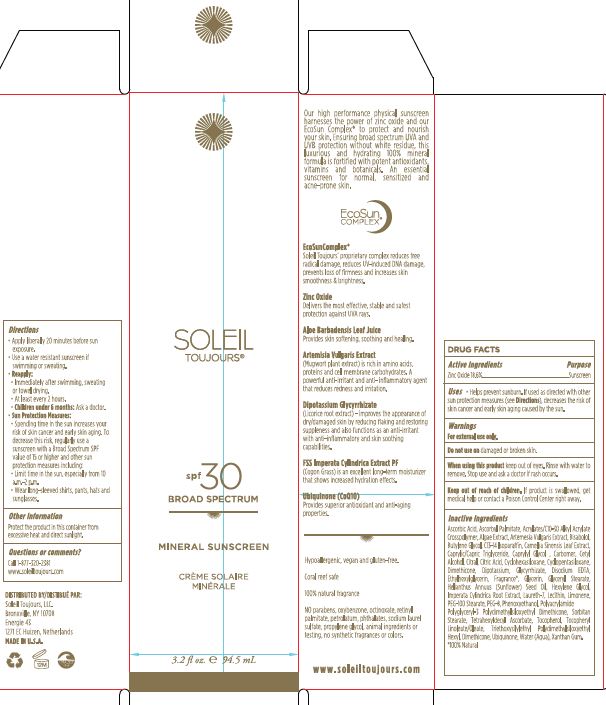 DRUG LABEL: Mineral Sunscreen Broad Spectrum SPF 30
NDC: 62742-4154 | Form: CREAM
Manufacturer: Allure Labs, Inc
Category: otc | Type: HUMAN OTC DRUG LABEL
Date: 20171212

ACTIVE INGREDIENTS: ZINC OXIDE 50.0 mg/1 mL
INACTIVE INGREDIENTS: ASCORBIC ACID; ASCORBYL PALMITATE; (C10-C30)ALKYL METHACRYLATE ESTER; ARTEMISIA VULGARIS ROOT; .BETA.-BISABOLOL; BUTYLENE GLYCOL; C13-14 ISOPARAFFIN; CAMELLIA SINENSIS FLOWER; MEDIUM-CHAIN TRIGLYCERIDES; CAPRYLYL GLYCOL; CARBOMER 934; CETYL ALCOHOL; CITRAL; CITRIC ACID MONOHYDRATE; CYCLOMETHICONE 6; CYCLOMETHICONE 5; DIMETHICONE; EDETATE DISODIUM; ETHYLHEXYLGLYCERIN; GLYCERIN; GLYCERYL STEARATE SE; SUNFLOWER OIL; HEXYLENE GLYCOL; IMPERATA CYLINDRICA ROOT; LAURETH-7; LECITHIN, SOYBEAN; LIMONENE, (+)-; PEG-100 STEARATE; POLYETHYLENE GLYCOL 400; PHENOXYETHANOL; SORBITAN MONOSTEARATE; TETRAHEXYLDECYL ASCORBATE; TOCOPHEROL; .ALPHA.-TOCOPHEROL LINOLEATE, D-; UBIQUINONE Q2; WATER; XANTHAN GUM

Drug Facts

ACTIVE INGREDIENT

Zinc Oxide - 18.6%

INDICATIONS AND USAGE

Helps prevent sunburn

if used as directed with other sun protection measures, decreases the risk of skin cancer and early skin aging caused by the sun.

WARNINGS

For external use only.

do not use on damaged or broken skin.

When using this product keep out of eyes. Rinse with water to remove.

Stop use and ask a doctor if rash occurs.

KEEP OUT OF REACH OF CHILDREN

if product is swallowed, get medical help or contact a Poison Control Center right away.

DOSAGE AND ADMINISTRATION

apply liberally 20 minutes before sun exposure.

use a water resistant sunscreen if swimming or sweating.

reapply:

immidiately aftr swimming, sweating or towel drying.

at least every 2 hours.

children under 6months: ask doctor

Sun protection measures:

Spending time in the sun increases your risk of skin cancer and early skin aging. To decrease the risk, regularly use a sunscreen with a Broad Spectrum SPF value of 15 or higher and other sun protector measures including:

limit time in the sun, especially from 10:00 am to 2:00 pm.

wear long sleaved shirts, pants, hats and sun glasses.

OTHER SAFETY INFORMATION

May stain or damage some fabrics or surfaces. Avoid long term storage above 40C (120F). Protect the product in this container from excessive heat and direct sunlight.

INACTIVE INGREDIENT

Ascorbic Acid, Ascorbyl Palmitate, Acrylates/C10-3- Alkyl Acrylate Crosspolymer, Algae Extract, Artemesia Vulgaris Extract, Bisabolol, Butylene Glycol, C13-14 Isoparaffin, Camellia Sinensis Leaf Extract, Caprylic/Capric Triglycerides, Caprylyl Glycol, Carbomer, Cetyl Alcohol, Citral, Citric Acid, Cyclohexasiloxane, Cyclopentasiloxane, Dimethicone, Dipotassium Glycyrrhizate, Disodium EDTA, Ethylhexylglycerin, Fragrance*, Glycerin, Glyceryl Stearate, Helianthus Annuus (Sunflower) Seed Oil, Hexylene Glycol, Imperata Cylindrica Root Extract, Laureth-7, Lecithin, Limonene, PEG-100 Stearate, PEG-8, Phenoxyethanol, Polyacrylamide Polyglyceryl-3 Polydimethylsiloxyethyl Dimethicone, Sorbitan Stearate, Tetrahexyldecyl Ascorbate, Tocopherol, Tocopheryl Linoleate/Oleate, Triethoxysilylethyl Polydimethylsiloxyethyl Hexyl Dimethicone, Obiquinone, Water (Aqua), Xanthan Gum. 100% Natural

PACKAGE LABEL

Distributed By:

The Soleil Group, LLC.

Bronxville, NY 10708

Energie 43

1271 EC Huizen, Netherlands

www.soleiltoujours.com

MADE IN USA